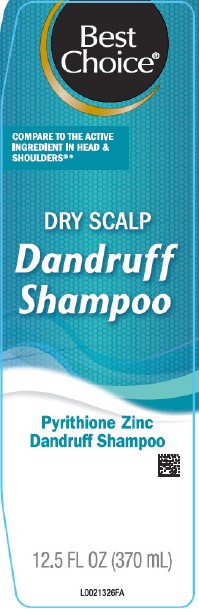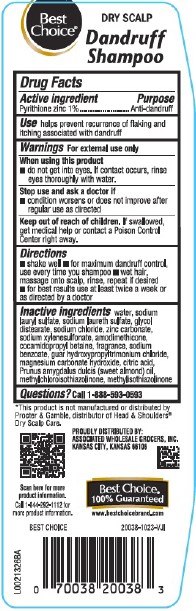 DRUG LABEL: Dry Scalp
NDC: 63941-952 | Form: SHAMPOO
Manufacturer: Valu Merchandisers Company
Category: otc | Type: HUMAN OTC DRUG LABEL
Date: 20260216

ACTIVE INGREDIENTS: PYRITHIONE ZINC 10 mg/1 mL
INACTIVE INGREDIENTS: WATER; SODIUM LAURYL SULFATE; SODIUM LAURETH SULFATE; GLYCOL DISTEARATE; SODIUM CHLORIDE; ZINC CARBONATE; SODIUM XYLENESULFONATE; AMODIMETHICONE (800 CST); COCAMIDOPROPYL BETAINE; SODIUM BENZOATE; GUAR HYDROXYPROPYLTRIMONIUM CHLORIDE (1.7 SUBSTITUENTS PER SACCHARIDE); MAGNESIUM CARBONATE HYDROXIDE; CITRIC ACID MONOHYDRATE; ALMOND OIL; METHYLCHLOROISOTHIAZOLINONE; METHYLISOTHIAZOLINONE

Best Choice 281.007/281AK,AN
Dandruff Shampoo, Dry Scalp

Claims

Best Choice®

DRY SCALP

Dandruff Shampoo

Active ingredient

Pyrithione zinc 1%

Purpose

Anti-dandruff

Use

helps prevent recurrence of flaking and itching associated with dandruff

Warnings

For external use only

When using this product

- do not get into eyes. If contact occurs, rinse eyes thoroughly with water.

Stop use and ask a doctor if

- condition worsens or does not improve after reqular use as directed

Keep out of reach of children.

If swallowed, get medical help or contact a Poison Control Center right away.

Directions

- shake well
- for maximum dandruff control, use every time you shampoo
- wet hair, massage onto scalp, rinse, repeat if desired
- for best results use at least twice a week or as directed by a doctor

inactive ingredients

water, sodium lauryl sulfate, sodium laureth sulfate, glycol distearate, sodium chloride, zinc carbonate, sodium xylenesulfonate, amodimethicone, cocamidopropyl betaine, fragrance, sodium benzoate, guar hydroxypropyltrimonium chloride, magnesium carbonate hydroxide, citric acid, Prunus amygdalus dulcis (sweet almond) oil, methylchloroisothiazolinone, methylisothiazolinone

Questions?

Call 1-888-593-0593

Disclaimer

*This product is not manufactured or distributed by Procter & Gamble, distributor of Head & Shoulders® Dry Scalp Care.

Adverse Reactions

PROUDLY DISTRIBUTED BY:

ASSOCIATED WHOLESALE GROCERS, INC.

KANSAS CITY, KS 66106

Scan here for more product information.

Call 1-844-292-1112 for more product information.

Best Choice®

100% Guaranteed

www.bestchoicebrand.com

Principal display panel

Best Choice®

COMPARE TO THE ACTIVE INGREDIENT IN HEAD & SHOULDERS®*

DRY SCALP

DANDRUFF

SHAMPOO

Pyrithione Zinc

Dandruff Shampoo

12.5 FL OZ (370 mL)